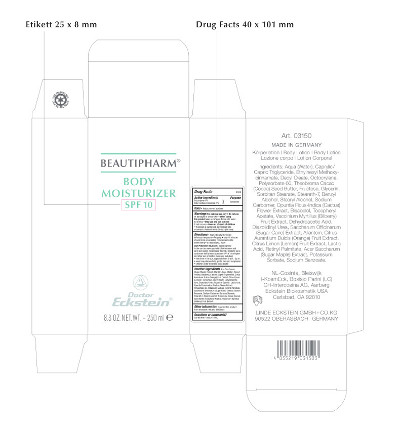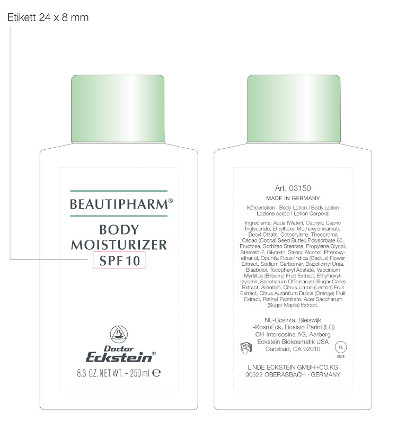 DRUG LABEL: Beautipharm Body Moisturizer
NDC: 6889-0315 | Form: CREAM
Manufacturer: Linde Eckstein GmbH + Co. KG
Category: otc | Type: HUMAN OTC DRUG LABEL
Date: 20161005

ACTIVE INGREDIENTS: OCTOCRYLENE 10 g/250 mL; OCTINOXATE 10 g/250 mL
INACTIVE INGREDIENTS: WATER 119.125 g/250 mL; MEDIUM-CHAIN TRIGLYCERIDES 25 g/250 mL; DECYL OLEATE 25 g/250 mL; POLYSORBATE 60 7.5 g/250 mL; THEOBROMA GRANDIFLORUM SEED BUTTER 7.5 g/250 mL; FRUCTOSE 7.5 g/250 mL; GLYCERIN 7.5 g/250 mL; SORBITAN MONOSTEARATE 7.5 g/250 mL; STEARETH-7 7.5 g/250 mL; BENZYL ALCOHOL 2.5 g/250 mL; STEARYL ALCOHOL 2.5 g/250 mL; CARBOMER HOMOPOLYMER TYPE C 2.5 g/250 mL; OPUNTIA FICUS-INDICA FLOWER 2.5 g/250 mL; LEVOMENOL 2.5 g/250 mL; .ALPHA.-TOCOPHEROL ACETATE, DL- 0.75 g/250 mL; BILBERRY 0.75 g/250 mL; DEHYDROACETIC ACID 0.75 g/250 mL; DIAZOLIDINYL UREA 0.25 g/250 mL; SUGARCANE 0.25 g/250 mL; ALLANTOIN 0.25 g/250 mL; ORANGE 0.075 g/250 mL; LEMON 0.075 g/250 mL; LACTIC ACID 0.075 g/250 mL; VITAMIN A PALMITATE 0.075 g/250 mL; ACER SACCHARUM BARK/SAP 0.025 g/250 mL; POTASSIUM SORBATE 0.025 g/250 mL; SODIUM BENZOATE 0.025 g/250 mL

Beautipharm® Body Moisturizer

Beautipharm® Body Moisturizer

SPF 10

8.3 OZ. NET.WT. – 250 ml

Art. 03150

MADE IN GERMANY

Körperlotion - Body Lotion – Body Lotion – Lozione corpo – Lotión Corporal

Ingredients: Aqua (Water), Caprylic Capric Triglyceride, Ethylhexyl Methoxycinnamate, Decyl Oleate, Octocrylene, Polysorbate 60, Theobroma Cacao (Cocoa) Seed Butter, Fructose, Glycerin, Sorbitan Stearate, Steareth-7, Benzyl Alcohol, Stearyl Alcohol, Sodium Carbomer, Opuntia Ficus-Indica (Cactus) Flower Extract, Bisabolol, Tocopheryl Acetate, Vaccinium Myrtillus (Bilberry) Fruit Extract, Dehydroacetic Acid, Diazolidinyl Urea, Saccharum Officinarum (Sugar Cane) Extract, Allantoin, Citrus Aurantium Dulcis (Orange) Fruit Extract, Citrus Limon (Lemon) Fruit Extract, Lactic Acid, Retinyl Palmitate, Acer Saccharum (Sugar Maple) Extract, Potassium Sorbate, Sodium Benzoate.

NL-Cosinta, Bleiswijk

KosmEck Italia – Bosisio Parini (LC)

CH-Intercosina AG, Aarberg

Eckstein Biokosmetik USA

Carlsbad, CA 92010

LINDE ECKSTEIN GMBH+CO.KG

90522 OBERASBACH · GERMANY

Drug Facts

Active Ingredients

Octocrylene 4%

Octyl methoxycinnamate 4%

Purpose

Sunscreen

Uses

• Helps prevent sunburn

Warnings For external use only

• Do not use on damaged or broken skin

• When using this product keep out of eyes. Rinse with water to remove

• Stop use and ask a doctor if rash occurs

• Keep out of reach of children

• If product is swallowed, get medical help or contact a Poison Control Center right away.

Directions

• Apply liberally 15 minutes before sun exposure

• Reapply:

• after 40 minutes of swimming or sweating

• immediately after towel drying

• at least every 2 hours

Sun Protection Measures.

Spending time in the sun increases your risk of skin cancer and early skin aging. To decrease this risk, regularly use a sunscreen with a broad spectrum SPF of 15 or higher and other sun protection measures including:

• limit time in the sun, especially from 10 a.m. - 2 p.m.

• wear long-sleeve shirts, pants, hats and sunglasses

• children under 6 months: ask a doctor

Inactive ingredients

Acer Saccharum (Sugar Maple) Extract, Allantoin, Aqua (Water), Benzyl Alcohol, Bisabolol, Caprylic/Capric Triglyceride, Citrus Aurantium Dulcis (Orange) Fruit Extract, Citrus Limon (Lemon) Fruit Extract, Decyl Oleate, Dehydroacetic Acid, Diazolidinyl Urea, Fructose, Glycerin, Lactic Acid, Opuntia Ficus-Indica (Cactus) Flower Extract, Polysorbate 60, Potassium Sorbate, Retinyl Palmitate, Saccharum Officinarum (Sugar Cane) Extract, Sodium Benzoate, Sodium Carbomer, Sorbitan Stearate, Steareth-7, Stearyl Alcohol, Theobroma Cacao (Cocoa) Seed Butter, Tocopheryl Acetate, Vaccinium Myrtillus (Bilberry) Fruit Extract

Other information

• protect this product from excessive heat and direct sun

Questions or comments?

Call toll free +888 345 1950

Beautipharm® Body Moisturizer

SPF 15

8.3 OZ. NET.WT. – 250 ml

Art. 03150

Made in Germany

Körperlotion - Body Lotion – Body Lotion – Lozione corpo – Lotión Corporal

Ingredients: Aqua (Water), Caprylic Capric Triglyceride, Ethylhexyl Methoxycinnamate, Decyl Oleate, Octocrylene, Polysorbate 60, Theobroma Cacao (Cocoa) Seed Butter, Fructose, Glycerin, Sorbitan Stearate, Steareth-7, Benzyl Alcohol, Stearyl Alcohol, Sodium Carbomer, Opuntia Ficus-Indica (Cactus) Flower Extract, Bisabolol, Tocopheryl Acetate, Vaccinium Myrtillus (Bilberry) Fruit Extract, Dehydroacetic Acid, Diazolidinyl Urea, Saccharum Officinarum (Sugar Cane) Extract, Allantoin, Citrus Aurantium Dulcis (Orange) Fruit Extract, Citrus Limon (Lemon) Fruit Extract, Lactic Acid, Retinyl Palmitate, Acer Saccharum (Sugar Maple) Extract, Potassium Sorbate, Sodium Benzoate.

NL-Cosinta, Bleiswijk

I-KosmEck, Bosisio Parini (LC)

CH-Intercosina AG, Aarberg

Eckstein Biokosmetik USA

Carlsbad, CA 92010

LINDE ECKSTEIN GMBH+CO.KG

90522 OBERASBACH · GERMANY